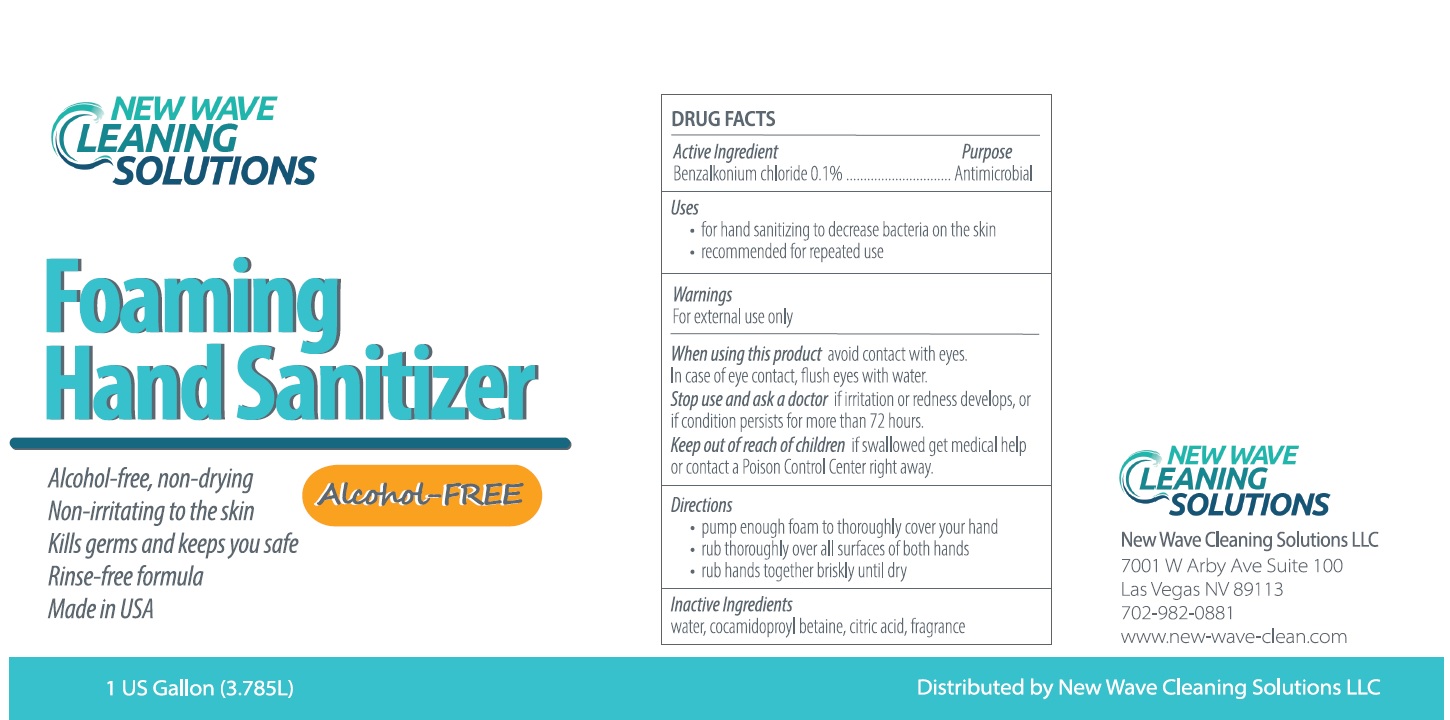 DRUG LABEL: New Wave Cleaning Solutions Foaming Hand Sanitizer
NDC: 80042-003 | Form: SOAP
Manufacturer: NEW WAVE CLEANING SOLUTIONS,LLC
Category: otc | Type: HUMAN OTC DRUG LABEL
Date: 20231023

ACTIVE INGREDIENTS: BENZALKONIUM CHLORIDE 1 mg/1 mL
INACTIVE INGREDIENTS: WATER; COCAMIDOPROPYL BETAINE; CITRIC ACID MONOHYDRATE

New Wave Cleaning Solutions Foaming Hand Sanitizer

Active Ingredient

Benzalkonium chloride 0.1%

Purpose

Antimicrobial

Uses

- for hand sanitizing to decrease bacteria on the skin
- recommended for repeated use

Warnings

For external use only

When using this product

avoid contact with eyes. In case of eye contact, flush eyes with water.

Stop use and ask a doctor

if irritation or redness develops, or if condition persists for more than 72 hours.

Keep out of reach of children

if swallowed get medical help or contact a Poison Control Center right away.

Directions

- pump enough foam to thoroughly cover your hand
- rub thoroughly over all surfaces of both hands
- rub hands together briskly until dry

Inactive Ingredients

water, cocamidopropyl betaine, citric acid, fragrance